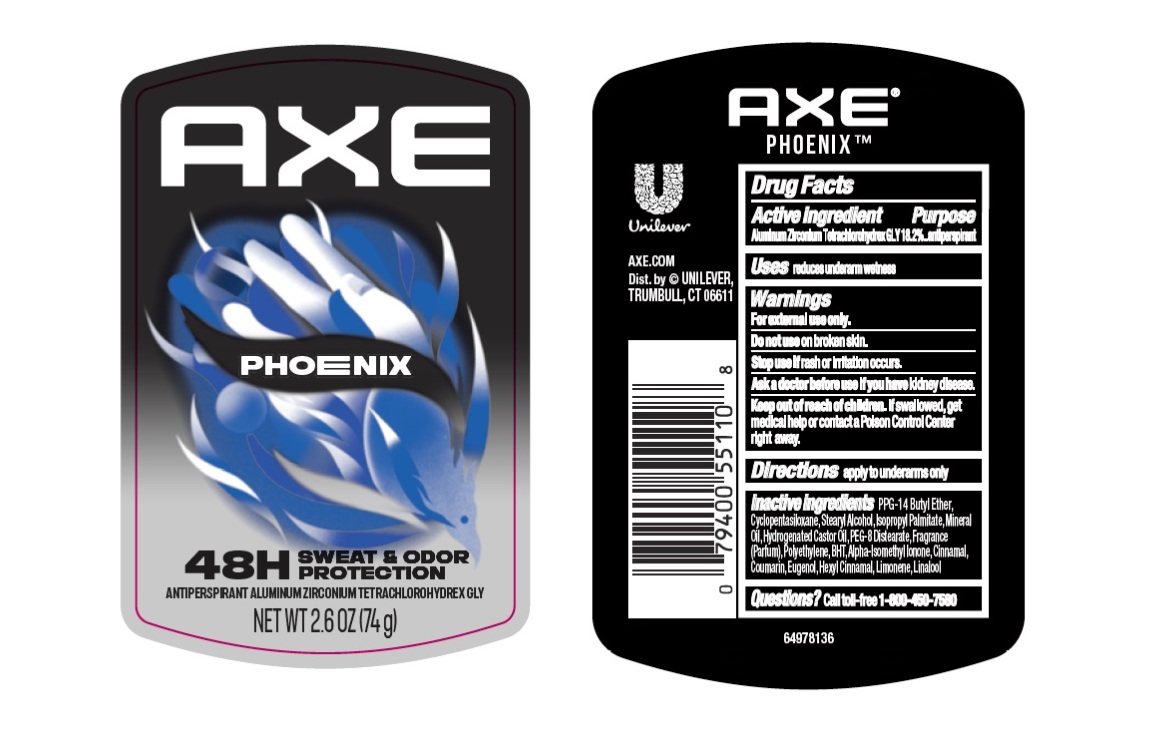 DRUG LABEL: Axe
NDC: 64942-2399 | Form: STICK
Manufacturer: Conopco d/b/a Unilever
Category: otc | Type: HUMAN OTC DRUG LABEL
Date: 20251121

ACTIVE INGREDIENTS: ALUMINUM ZIRCONIUM TETRACHLOROHYDREX GLY 18.2 g/100 g
INACTIVE INGREDIENTS: PPG-14 BUTYL ETHER; CINNAMAL; EUGENOL; PEG-8 DISTEARATE; STEARYL ALCOHOL; HEXYL CINNAMAL; LIMONENE, (+/-)-; LINALOOL, (+/-)-; CYCLOPENTASILOXANE; POLYETHYLENE; ISOPROPYL PALMITATE; MINERAL OIL; HYDROGENATED CASTOR OIL; BHT; ALPHA-ISOMETHYL IONONE; COUMARIN

Axe Phoenix 48H Sweat and Odor Protection Antiperspirant Deodorant Stick

DESCRIPTION

Axe Phoenix 48H Sweat and Odor Protection Antiperspirant Deodorant Stick

ACTIVE INGREDIENT

Aluminum Zirconium Tetrachlorohydrex GLY 18.2%

PURPOSE

Antiperspirant

INDICATIONS AND USAGE

reduces underarm wetness

WARNINGS

For external use only.
Do not use on broken skin. Stop use if rash or irritation occurs. Ask a doctor beforeuse if you have kidney disease.

Keep out of reach of children. If swallowed,get medical help or contact a Poison Control Center right away.

DOSAGE AND ADMINISTRATION

apply to underarms only

INACTIVE INGREDIENT

PPG-14 Butyl Ether,Cyclopentasiloxane,Stearyl Alcohol,Isopropyl Palmitate,Mineral Oil,Hydrogenated Castor Oil,PEG-8 Distearate,Fragrance (Parfum),Polyethylene,BHT,Alpha-Isomethyl Ionone,Cinnamal, Coumarin,Eugenol,Hexyl Cinnamal,Limonene,Linalool

QUESTIONS

Call toll-free 1-800-450-7580